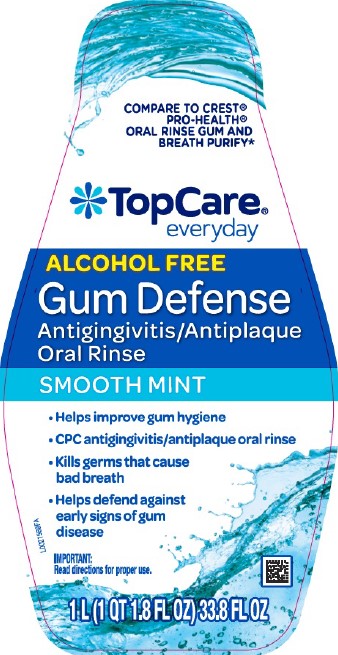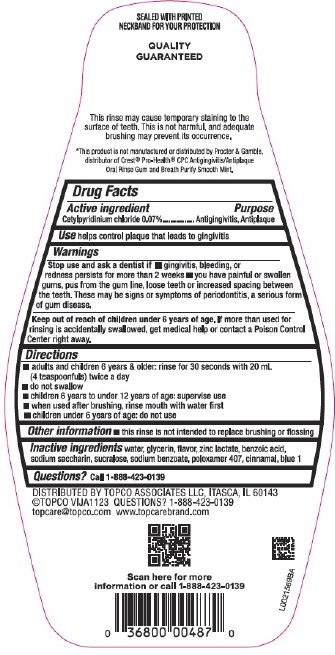 DRUG LABEL: Antigingivitis/Antiplaque
NDC: 76162-090 | Form: MOUTHWASH
Manufacturer: Topco Associates LLC
Category: otc | Type: HUMAN OTC DRUG LABEL
Date: 20260213

ACTIVE INGREDIENTS: CETYLPYRIDINIUM CHLORIDE 0.7 mg/1 mL
INACTIVE INGREDIENTS: GLYCERIN; WATER; ZINC LACTATE; BENZOIC ACID; SACCHARIN SODIUM; SUCRALOSE; SODIUM BENZOATE; POLOXAMER 407; CINNAMALDEHYDE; FD&C BLUE NO. 1

Top Care D00.001/D00AA
Alcohol-Free Gum Defense Mouthwash

Tamper Evident Statement

SEALED WITH PRINTED NECKBAND FOR YOUR PROTECTION

Disclaimer

QUALITY GUARANTEED

This rinse may cause temporary staining to the surface of teeth. This is not harmful, and adequate brushing may prevent its occurance.

*This product is not manufactured or distributed by Procter & Gamble, distributor of Crest® Pro-Health® CPC Antigingivitis/Antiplaque Oral Rinse Gum and Breath Purify Smooth Mint.

Active Ingredient

Cetylpyridinium Chloride 0.07%

Purpose

Antigingivitis, Antiplaque

Use

helps control plaque that leads to gingivitis

Warnings

For this product

Stop use and ask a dentist if

- gingivitis, bleeding, or redness persists for more than 2 weeks
- you have painful or swollen gums, pus from the gum line, loose teeth or increased spacing between the teeth. These may be signs or symptoms of periodontitis, a serious form of gum disease.

Keep out of reach of children under 6 years of age.

If more than used for rinsing is accidentally swallowed, get medical help or contact a Poison Control Center right away.

Directions

- adults and children 6 years & older: rinse for 30 seconds with 20 mL (4 teaspoonfuls) twice a day
- do not swallow
- children 6 years to under 12 years of age: supervise use
- when used after brushing, rinse mouth with water first
- children under 6 years of age: do not use

Other information

- this rinse is not intended to replace brushing or flossing

Inactive ingredients

water, glycerin, flavor, zinc lactate, benzoic acid, sodium saccharin, sucralose, sodium benzoate, poloxamer 407, cinnamal, blue 1

Questions?

Call 1-888-423-0139

Adverse reaction

DISTRIBUTED BY TOPCO ASSOCIATED LLC, ITASCA, IL 60143

©TOPCO VIJA1123 QUESTIONS? 1-888-423-0139

topcare@topco.com www.topcarebrand.com

Scan here for more information or call 1-888-423-0139

Principal Display Panel

COMPARE TO CREST® PRO-HEALTH® ORAL RINSE GUM AND BREATH PURIFY*

TopCare® everyday

ALCOHOL FREE

Gum Defense

Antigingivitis/Antiplaque

Oral Rinse

SMOOTH MINT

- Helps improve gum hygiene
- CPC antigingivitis/antiplaque oral rinse
- kills germs that cause bad breath
- helps defend against early signs of gum disease

IMPORTANT: Read directions for proper use.

1 L (1 QT 1.8 FL OZ) 33.8 FL OZ